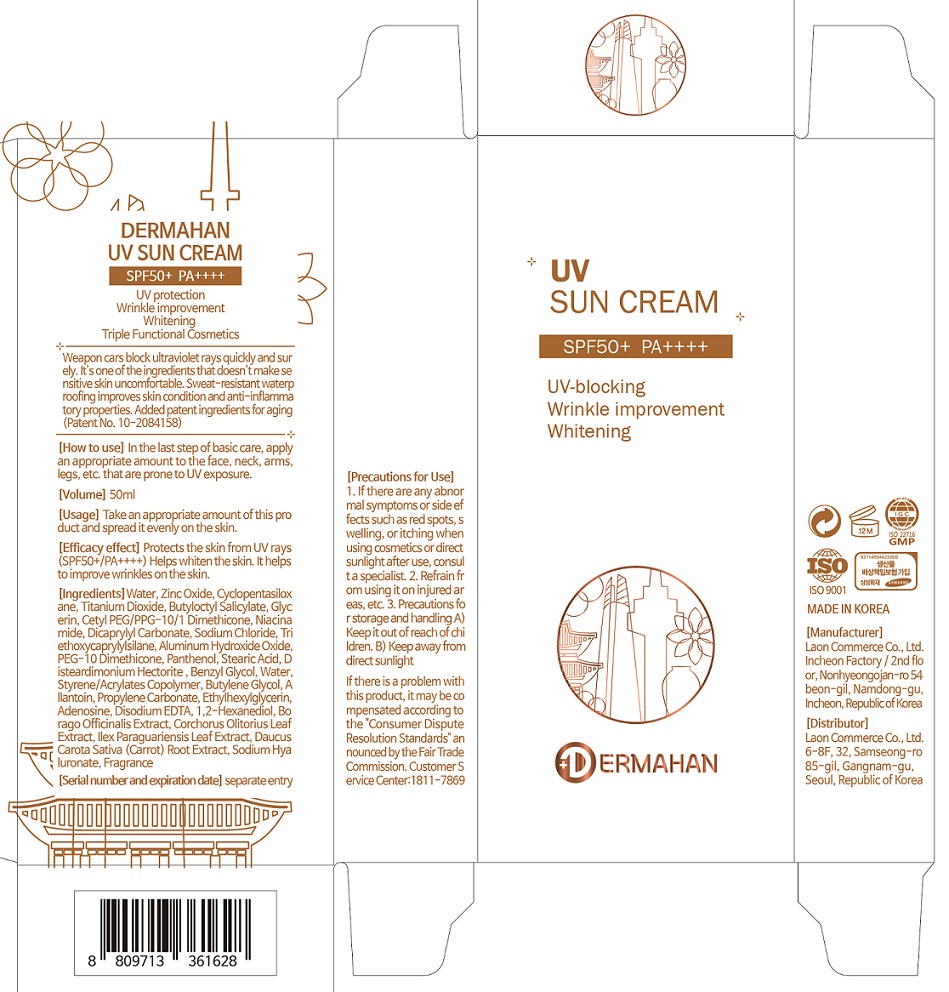 DRUG LABEL: DERMAHAN UV SUN
NDC: 82083-0016 | Form: CREAM
Manufacturer: LAON COMMERCE co ltd
Category: otc | Type: HUMAN OTC DRUG LABEL
Date: 20230417

ACTIVE INGREDIENTS: ADENOSINE 0.04 g/100 mL; NIACINAMIDE 2 g/100 mL
INACTIVE INGREDIENTS: WATER

ACTIVE INGREDIENT

Niacinamide, Adenosine

INACTIVE INGREDIENT

Water
Zinc Oxide
Cyclopentasiloxane
Titanium Dioxide
Butyloctyl Salicylate
Glycerin
Cetyl PEG/PPG-10/1 Dimethicone
Niacinamide
Dicaprylyl Carbonate
Sodium Chloride
Triethoxycaprylylsilane
Aluminum Hydroxide Oxide
PEG-10 Dimethicone
Panthenol
Stearic Acid
Disteardimonium Hectorite
Benzyl Glycol
Water
Styrene/Acrylates Copolymer
Butylene Glycol
Allantoin
Propylene Carbonate
Ethylhexylglycerin
Adenosine
Disodium EDTA
1,2-Hexanediol
Borago Officinalis Extract
Corchorus Olitorius Leaf Extract
Ilex Paraguariensis Leaf Extract
Daucus Carota Sativa (Carrot) Root Extract
Sodium Hyaluronate
Fragrance

PURPOSE

skin protect

KEEP OUT OF REACH OF THE CHILDREN

INDICATIONS AND USAGE

In the last step of basic care, apply an appropriate amount to the face, neck, arms, legs, etc. that are prone to UV exposure.

WARNINGS

1. If there are any abnormal symptoms or side effects such as red spots, swelling, or itching when using cosmetics or direct sunlight after use, consult a specialist.

2. Refrain from using it on injured areas, etc.

3. Precautions for storage and handling A) Keep it out of reach of children. B) Keep away from direct sunlight

3. Protects the skin from UV rays(SPF50+/PA++++) Helps whiten the skin. It helps to improve wrinkles on the skin.

DOSAGE AND ADMINISTRATION

topical use only